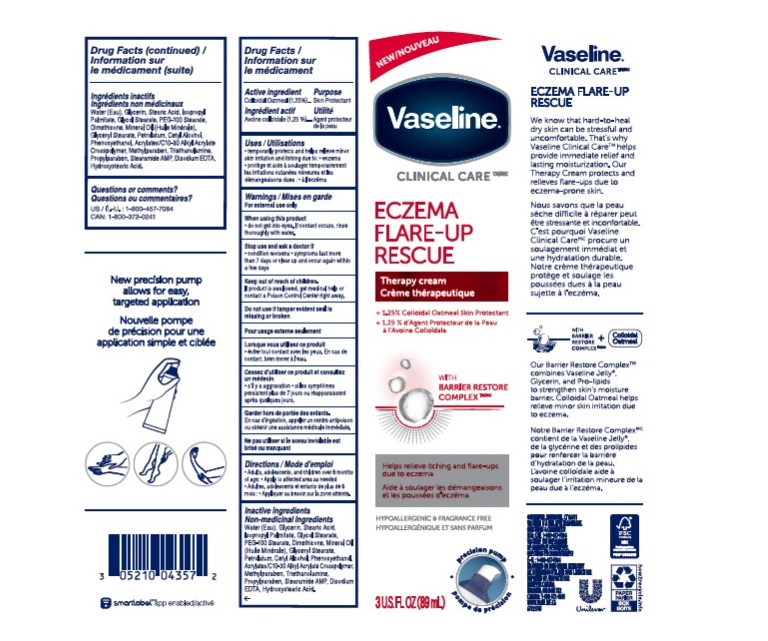 DRUG LABEL: Vaseline
NDC: 64942-1872 | Form: CREAM
Manufacturer: Conopco, Inc. d/b/a/ Unilever
Category: otc | Type: HUMAN OTC DRUG LABEL
Date: 20241107

ACTIVE INGREDIENTS: OATMEAL 1.25 g/100 mL
INACTIVE INGREDIENTS: WATER; GLYCERIN; STEARIC ACID; ISOPROPYL PALMITATE; GLYCOL STEARATE; DIMETHICONE; GLYCERYL MONOSTEARATE; PETROLATUM; CETYL ALCOHOL; PHENOXYETHANOL; METHYLPARABEN; CARBOMER INTERPOLYMER TYPE A (ALLYL SUCROSE CROSSLINKED); TROLAMINE; PROPYLPARABEN; STEARAMIDE AMP; EDETATE DISODIUM; PEG-100 STEARATE; MINERAL OIL; 12-HYDROXYSTEARIC ACID

Vaseline Clinical Care Eczema Flare-Up Rescue Therapy Cream

Description

VASELINE CLINICAL CARE ECZEMA FLARE-UP RESCUE THERAPY CREAM - (colloidal oatmeal) cream

Drug Facts

Active ingredient
Colloidal Oatmeal (1.25%)

Purpose

Skin Protectant

Uses

temporarily protects and helps relieve minor skin irritation and itching due to:

- eczema

Warnings

For external use only
When using this product do not get into eyes. If contact occurs, rinse thoroughly with water.
Stop use and ask a doctor if

- condition worsens
- symptoms last more than 7 days or clear up and occur again within a few days

Keep out of reach of children. If product is swallowed, get medical help or contact a Poison Control Center right away.

Directions

Adults, adolescents, and children over 6 months of age:

- Apply to affected area as needed

Inactive ingredients

Water (Eau), Glycerin, Stearic Acid, Isopropyl Palmitate, Glycol Stearate, PEG-100 Stearate, Dimethicone, Mineral Oil (Huile Minerale), Glyceryl Stearate, Petrolatum, Cetyl Alcohol, Phenoxyethanol, Acrylates/C10-30 Alkyl Acrylate Crosspolymer, Methylparaben, Triethanolamine, Propylparaben, Stearamide AMP, Disodium EDTA, Disodium EDTA, Hydroxystearic Acid.

Questions or comments?

1-800-457-7084